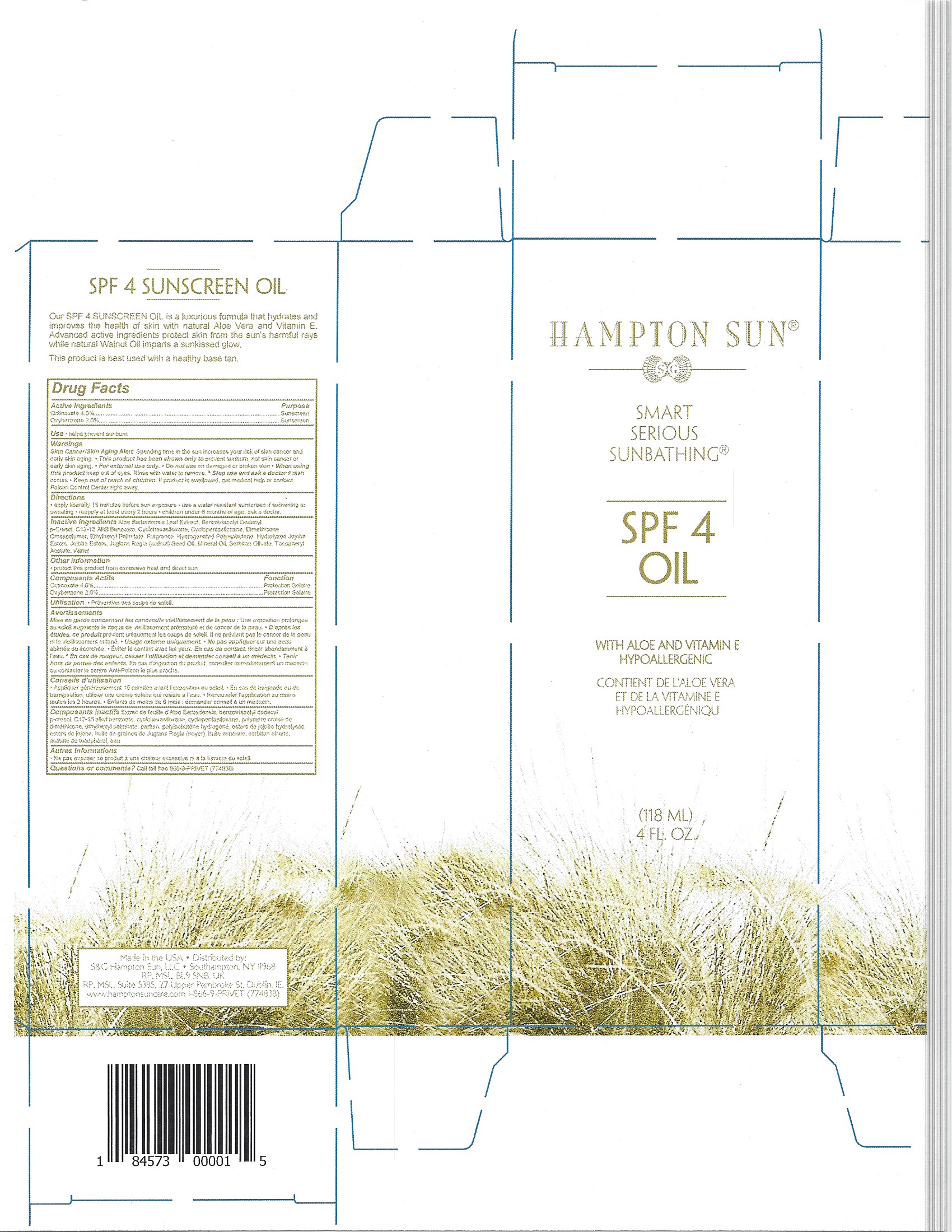 DRUG LABEL: HAMPTON SUN
NDC: 87170-001 | Form: GEL
Manufacturer: Hampton Sun
Category: otc | Type: HUMAN OTC DRUG LABEL
Date: 20251024

ACTIVE INGREDIENTS: OCTINOXATE 4 g/100 g; OXYBENZONE 2 g/100 g
INACTIVE INGREDIENTS: WATER; ALOE; BENZOTRIAZOLYL DODECYL P-CRESOL; DIMETHICONE CROSSPOLYMER (450000 MPA.S AT 12% IN CYCLOPENTASILOXANE); WALNUT OIL; MINERAL OIL; ETHYLHEXYL PALMITATE; SORBITAN OLIVATE; C12-15 ALCOHOLS; DIMETHICONE/VINYL DIMETHICONE CROSSPOLYMER (SOFT PARTICLE); HYDROLYZED JOJOBA ESTERS (POTASSIUM SALTS)

HAMPTON SUN SPF 4 SUNSCREEN OIL

Active Ingredients:

Octinoxate – 4.00%

Oxybenzone - 2.00%

PURPOSE

Octinoxate – 4.00%..................Sunscreen

Oxybenzone - 2.00%...............Sunscreen

INDICATIONS AND USAGE

Uses • Helps prevent sunburn

Warnings

Skin cancer/Skin Aging alert

For external use only

Do not use on Damage or broken skin

When using this product keep out of eyes. Rinse with water to remove.

Stop use and ask a doctor if rash occurs.

Keep out of reach of children. If swallowed, get medical help or contact a Poison Control Center immediately.

DIRECTIONS

• Apply liberally 15 minutes before sun exposure.

• Use water resistant sunscreen if swimming or sweating

• Reapply at least every 2 hours

• Children under 6 months of age: ask a doctor

Inactive Ingredients:

Aloe Barbadensis Leaf Extract, Benzotriazolyl Dodecyl p-Cresol, C12-15 Alkyl Benzoate, Cyclohexasiloxane, Cyclopentasiloxane

Dimethicone Crosspolymer, Ethylhexyl Palmitate, Fragrance, Hydrogenated Polyisobutene, Hydrolyzed Jojoba Esters, Jojoba Esters, Juglans Regia (Walnut) Seed Oil, Mineral Oil, Sorbitan Olivate, Tocopheryl Acetate, Water